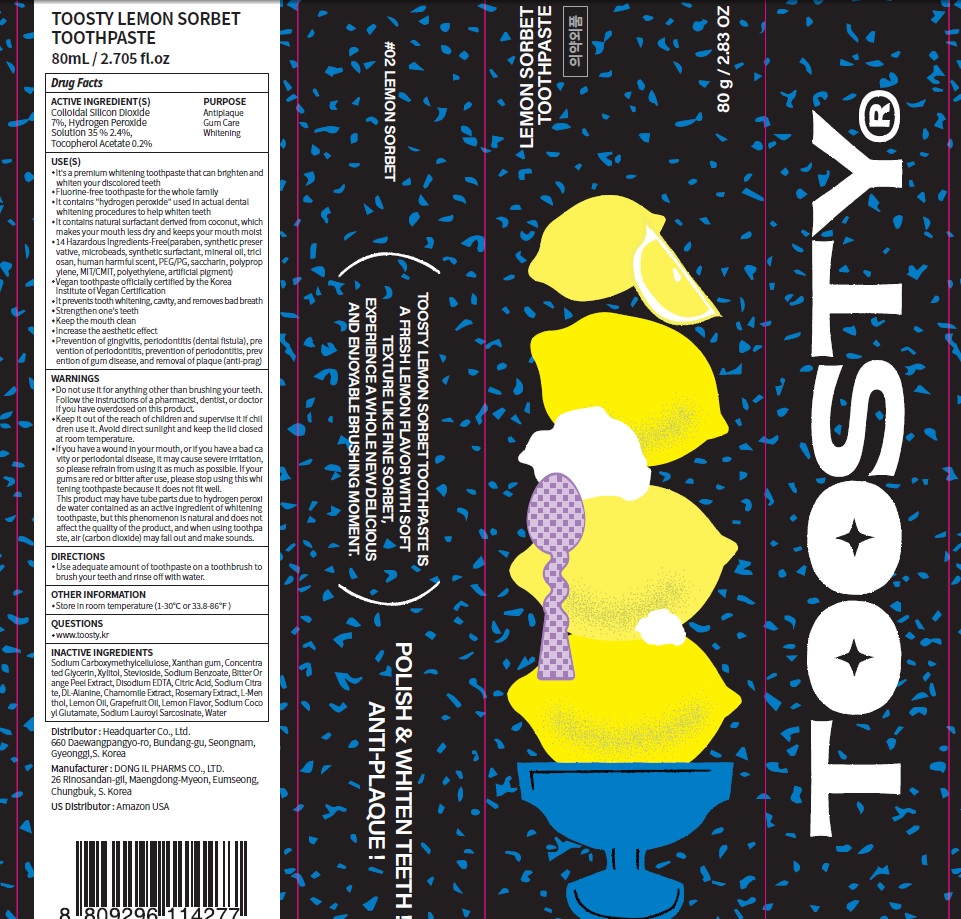 DRUG LABEL: Toosty Lemon Sorbet Toothpaste
NDC: 82662-040 | Form: PASTE, DENTIFRICE
Manufacturer: Headquarter Co., Ltd
Category: otc | Type: HUMAN OTC DRUG LABEL
Date: 20230726

ACTIVE INGREDIENTS: Silicon Dioxide 7.0 g/100 g; HYDROGEN PEROXIDE 2.4 g/100 g; .ALPHA.-TOCOPHEROL ACETATE 0.2 g/100 g
INACTIVE INGREDIENTS: CARBOXYMETHYLCELLULOSE SODIUM, UNSPECIFIED; Xanthan gum; Glycerin

ACTIVE INGREDIENTS

Colloidal Silicon Dioxide 7%
Hydrogen Peroxide Solution (35 %) 2.4%
Tocopherol Acetate 0.2%

INACTIVE INGREDIENTS

Sodium Carboxymethylcellulose, Xanthan gum, Concentrated Glycerin, Xylitol, Stevioside, Sodium Benzoate, Bitter Orange Peel Extract, Disodium EDTA, Citric Acid, Sodium Citrate, DL-Alanine, Chamomile Extract, Rosemary Extract, L-Menthol, Lemon Oil, Grapefruit Oil, Lemon Flavor, Sodium Cocoyl Glutamate, Sodium Lauroyl Sarcosinate, Water

PURPOSE

Antiplaque
Gum Care
Whitening

WARNINGS

■ Do not use it for anything other than brushing your teeth. Follow the instructions of a pharmacist, dentist, or doctor if you have overdosed on this product.
■ Keep it out of the reach of children and supervise it if children use it. Avoid direct sunlight and keep the lid closed at room temperature.
■ If you have a wound in your mouth, or if you have a bad cavity or periodontal disease, it may cause severe irritation, so please refrain from using it as much as possible. If your gums are red or bitter after use, please stop using this whitening toothpaste because it does not fit well. This product may have tube parts due to hydrogen peroxide water contained as an active ingredient of whitening toothpaste, but this phenomenon is natural and does not affect the quality of the product, and when using toothpaste, air (carbon dioxide) may fall out and make sounds.

KEEP OUT OF REACH OF CHILDREN

Keep it out of the reach of children and supervise it if children use it.

Uses

■ It's a premium whitening toothpaste that can brighten and whiten your discolored teeth
■ Fluorine-free toothpaste for the whole family
■ It contains "hydrogen peroxide" used in actual dental whitening procedures to help whiten teeth
■ It contains natural surfactant derived from coconut, which makes your mouth less dry and keeps your mouth moist
■ 14 Hazardous Ingredients-Free (paraben, synthetic preservative, microbeads, synthetic surfactant, mineral oil, triclosan, human harmful scent, PEG/PG, saccharin, polypropylene, MIT/CMIT, polyethylene, artificial pigment)
■ Vegan toothpaste officially certified by the Korea Institute of Vegan Certification
■ It prevents tooth whitening, cavity, and removes bad breath
■ Strengthen one's teeth
■ Keep the mouth clean
■ Increase the aesthetic effect
■ Prevention of gingivitis, periodontitis (dental fistula), prevention of periodontitis, prevention of periodontitis, prevention of gum disease, and removal of plaque (anti-plaque)

Directions

■ Use adequate amount of toothpaste on a toothbrush to brush your teeth and rinse off with water.

Other Information

■ Store in room temperature (1-30℃ or 33.8-86℉)

Questions

■ www.toosty.kr